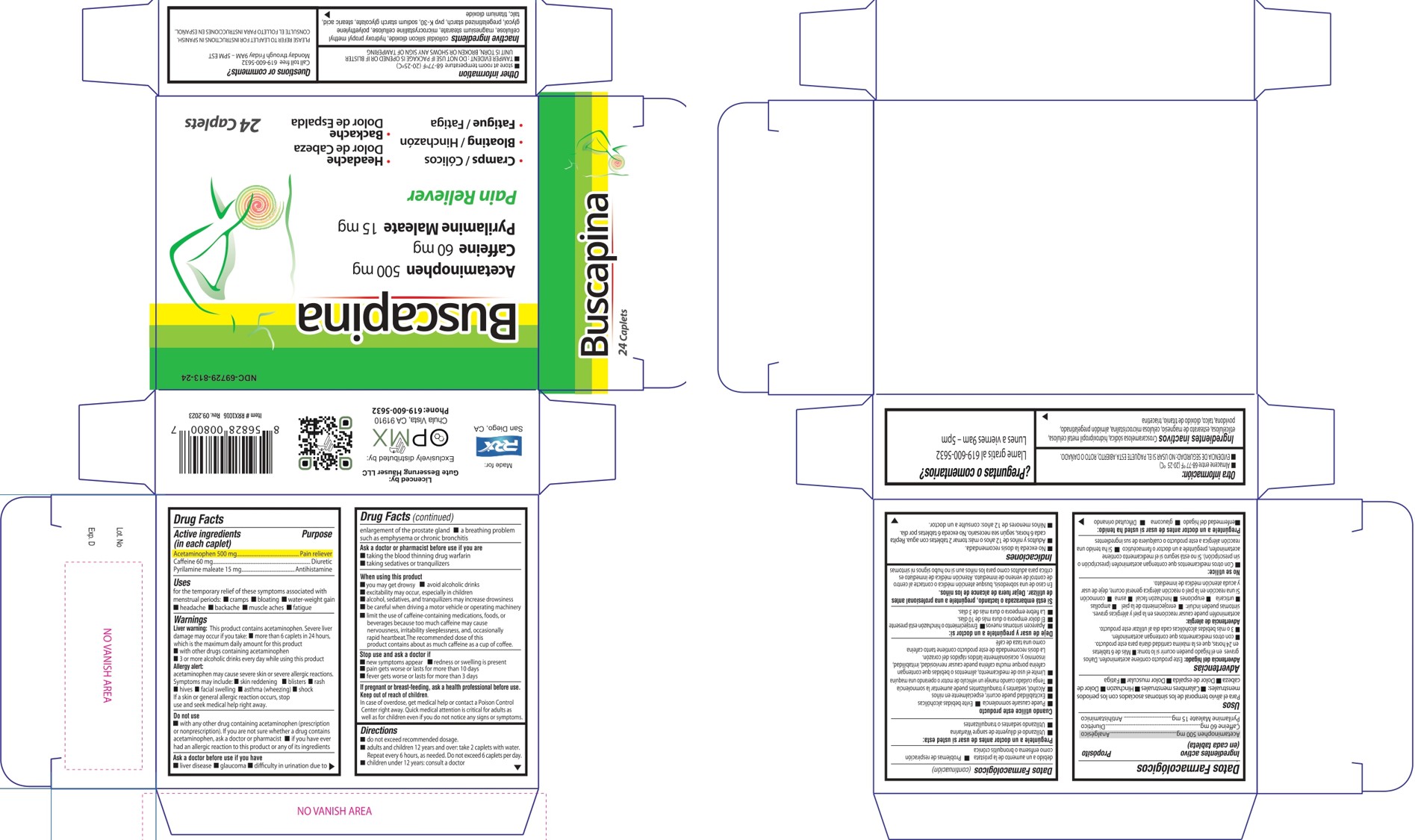 DRUG LABEL: Buscapina
NDC: 69729-813 | Form: TABLET, FILM COATED
Manufacturer: OPMX LLC
Category: otc | Type: HUMAN OTC DRUG LABEL
Date: 20251112

ACTIVE INGREDIENTS: PYRILAMINE MALEATE 500 mg/1 1; ACETAMINOPHEN 500 mg/1 1; CAFFEINE 60 mg/1 1
INACTIVE INGREDIENTS: SILICON DIOXIDE; POVIDONE K30; STEARIC ACID; STARCH, CORN; POLYETHYLENE GLYCOL, UNSPECIFIED; TALC; HYPROMELLOSE, UNSPECIFIED; SODIUM STARCH GLYCOLATE TYPE A; MICROCRYSTALLINE CELLULOSE; MAGNESIUM STEARATE; TITANIUM DIOXIDE

Buscapina NEW

Drug Facts

Active ingredients (in each caplet)

Acetaminophen 500 mg

Caffeine 60 mg

Pyrilamine maleate 15 mg

Purpose

Active ingredients (in each caplet) | Purpose
Acetaminophen 500 mg | Pain reliever
Caffeine 60 mg | Diuretic
Pyrilamine maleate 15 mg | Antihistamine

Uses

for the temporary relief of these symptoms associated with menstrual periods:

- cramps
- bloating
- water-weight gain
- headache
- backache
- muscle aches
- fatigue

Warnings

Liver warning: This product contains acetaminophen. Severe liver damage may occur if you take:

more than 6 tablets in 24 hours, which is the maximum daily amount for this product
with other drugs containing acetaminophen
3 or more alcoholic drinks every day while using this product.
Allergy warning: Acetaminophen may cause severe skin or severe allergic reactions. Symptoms may include:

- skin reddening
- blisters
- rash
- hives
- facial swelling
- asthma (wheezing)
- shock
- If a skin or general allergic reaction occurs, stop use and seek medical help right away.

Do not use

with any other drug containing acetaminophen (prescription or nonprescription). If you are not sure whether a drug contains acetaminophen, ask a doctor or pharmacist. if you have ever had an allergic reaction to this product or any of its ingredients

Ask a doctor before use if you have

- liver disease
- glaucoma
- difficulty un rination due to the enlargement of the prostate gland
- a breathing problem sucha as emphysema or chronic bronchitis

Ask a doctor or pharmacist before use if you are

- taking the blood thinning drug warfarin
- taking sedatives or tranquilizers

When using this product

- you may get drowsy
- avoid alcoholic drinks
- excitability may occur, especially in children
- alcohol, sedatives, and tranquilizers may increase drowsiness
- be careful when driving a motor vehicle or operating machinery
- limit the use of caffeine-containing medications, foods or beverages because too much caffeine may cause nervousness, irritability, sleeplessness, and occasionally rapid heartbeat. The recommended dose of this product contains aboout as much caffeine as a cup of coffee.

Stop use and ask a doctor if

- new symptoms appear
- redness or swelling is present
- pain gets worse or lasts for more than 10 days
- fever gets worse or lasts for more than 3 days

If pregnant or breast-feeding

ask a health professional before use

Keep out of reach of children

In case of overdose

get medical help or contact a Poison Control Center right away. Quick medical attention is critical for adults as well as for children even if you do not notice any signs or symtoms.

Directions

- do not exceed recommended dosage
- adults and children 12 years and over; take 2 caplets with water. Repeat every 6 hours, as needed. Do not exceed 6 caplets per day.
- children under 12 years: consult a doctor

Other information

- Store at room temperature 68-77°F (20-25°C)
- TAMPER EVIDENT: DO NOT USE IF PACKAGE IS OPENED OR IF BLISTER UNIT IS TORN, BROKEN OR SHOWS ANY SIGN OF TAMPERING

Inactive ingredientes

colloidal silicon dioxide,

hydroxy propyl methyl cellulose,

magnesium stearate,

microcrystalline cellulose,

polyethylene glycol,

pregelatinized starch,

pvp K-30,

sodium starch glycolate,

stearic acid,

talc,

titanium dioxide.

Questions?

Call toll free 619-600-5632

Monday through Friday 9AM-5PM EST

PLEASE REFER TO LEAFLET INSTRUCTUIONS IN SPANISH

CONSULTE EL FOLLETO PARA INSTRUCCIONES EN ESPAÑOL

PACKAGE LABEL

NDC-69729-131-24

Buscapina

Acetaminophen 500 mg

Caffeine 60mg

Pyrilamine Maleate 15mg

Pain Reliever

- Cramps/Cólicos
- Bloating/Hinchazón
- Fatigue/Fatiga
- Headache/ Dolor de cabeza
- Backache/Dolor de espalda

24 Caplets